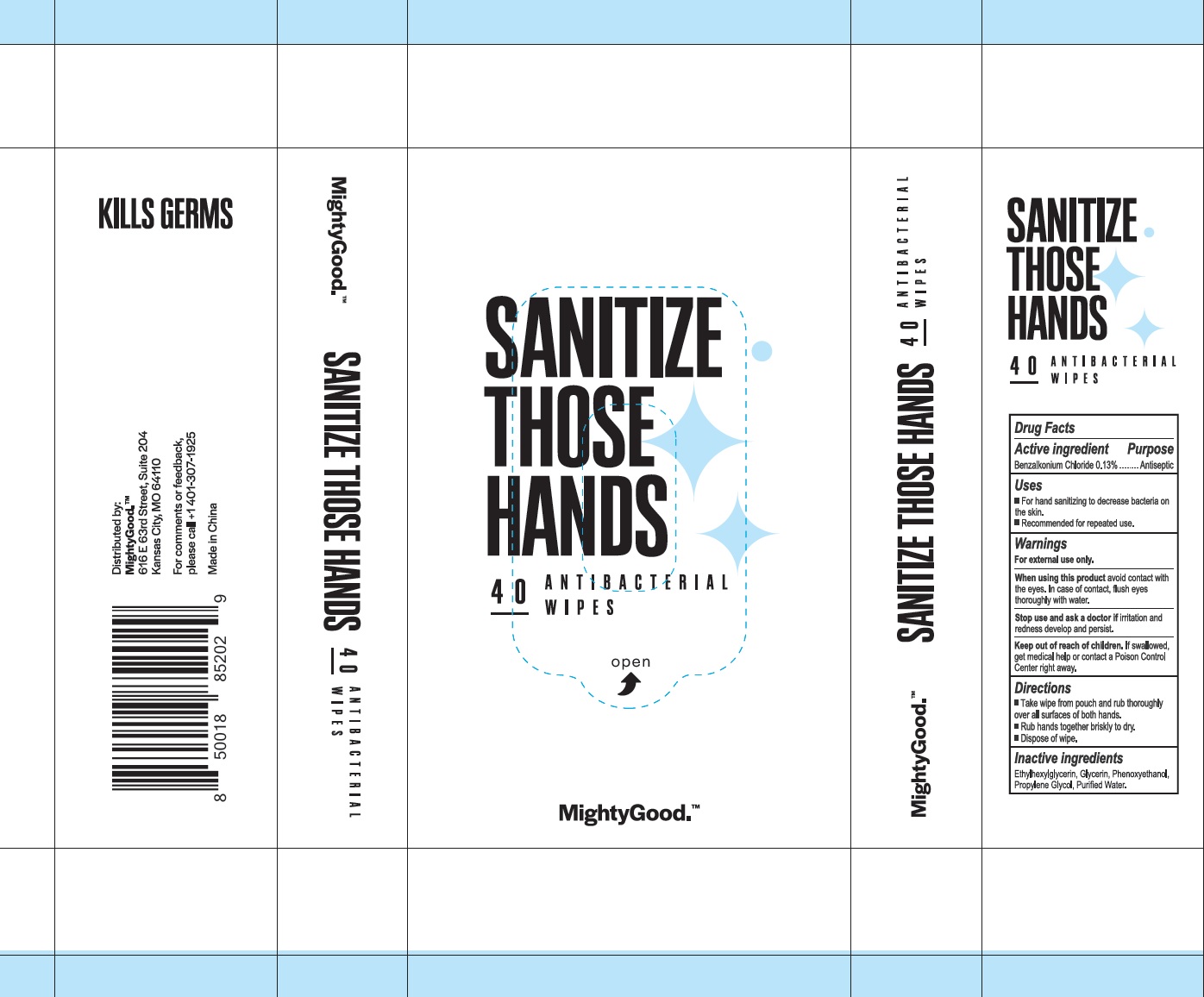 DRUG LABEL: Sanitize Those Hands 40 Antibacterial Wipes
NDC: 71734-324 | Form: SWAB
Manufacturer: JIANGMEN SHUIZIRUN SANITARY ARTICLES CO., LTD.
Category: otc | Type: HUMAN OTC DRUG LABEL
Date: 20200819

ACTIVE INGREDIENTS: benzalkonium chloride 0.13 g/100 g
INACTIVE INGREDIENTS: water; GLYCERIN; ETHYLHEXYLGLYCERIN; PHENOXYETHANOL; PROPYLENE GLYCOL

DRUG FACTS

Active Ingredient

Benzalkonium Chloride .......... 0.13 %

Purpose

Antiseptic

Uses:

For hand sanitizing to decrease bacteria on the skin.

Recommended for repeated use.

Warnings

For external use only.

When using this product avoid contact with the eyes .In case of contact, flush eyes thoroughly with water .

Stop use and ask a doctor if Irritation and redness develop and persist.

Keep out of reach of children.

if swallowed get medical help or contact a Poison Control Center right away.

Directions

Take wipe from pouch and rub thoroughly over all surfaces of both hands.

Rub hands together briskly to dry.

Dispose of wipe.

Inactive Ingredients:

Ethylhexylglycerin, Glycerin, Phenoxyethanol, Propylene Glycol, Purified Water